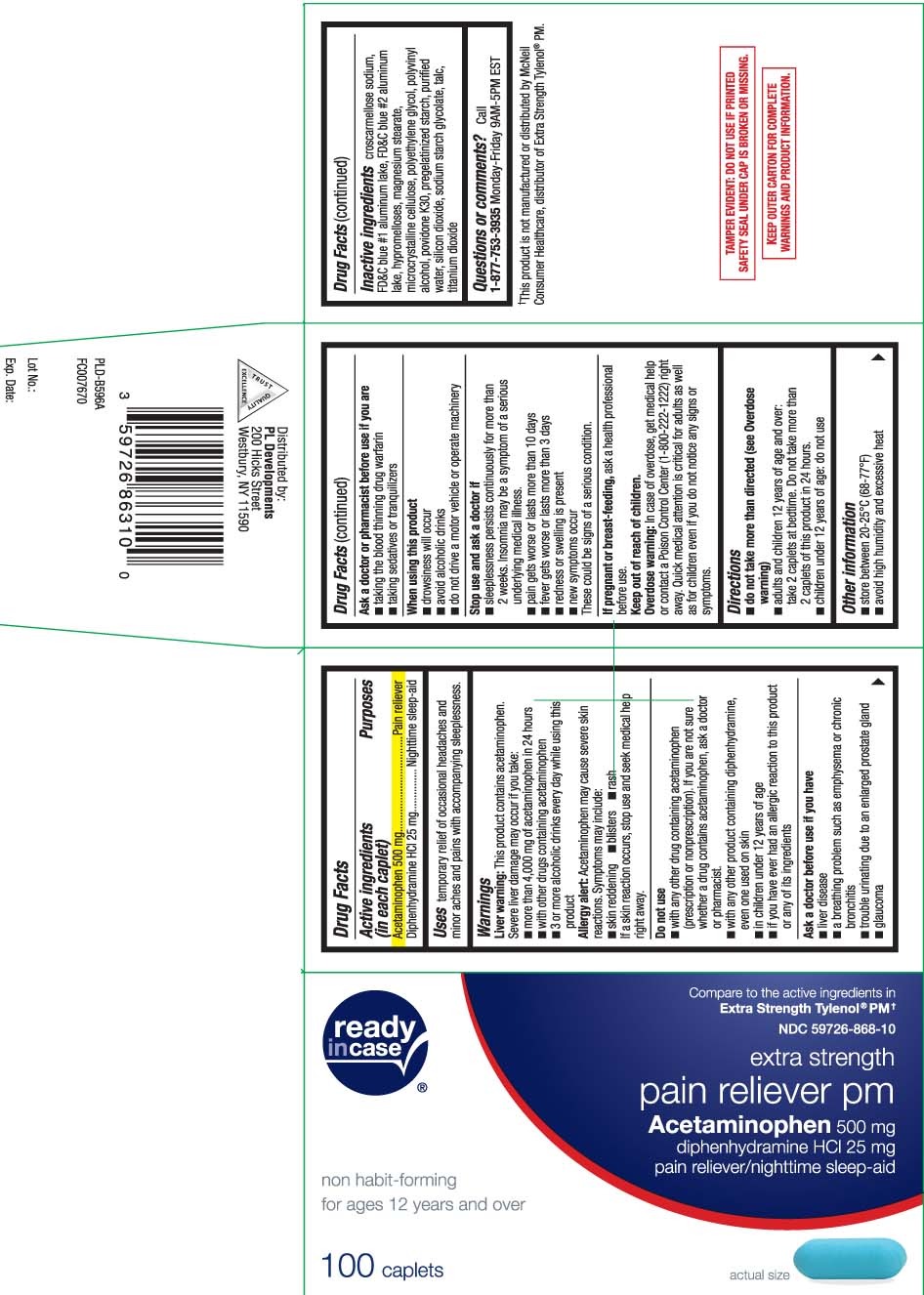 DRUG LABEL: Pain Reliever PM
NDC: 59726-868 | Form: TABLET, COATED
Manufacturer: P & L Development, LLC
Category: otc | Type: HUMAN OTC DRUG LABEL
Date: 20251211

ACTIVE INGREDIENTS: ACETAMINOPHEN 500 mg/1 1; DIPHENHYDRAMINE HYDROCHLORIDE 25 mg/1 1
INACTIVE INGREDIENTS: CROSCARMELLOSE SODIUM; FD&C BLUE NO. 1; FD&C BLUE NO. 2; HYPROMELLOSES; MAGNESIUM STEARATE; MICROCRYSTALLINE CELLULOSE; POLYETHYLENE GLYCOL, UNSPECIFIED; POLYVINYL ALCOHOL, UNSPECIFIED; POVIDONE K30; STARCH, CORN; WATER; SILICON DIOXIDE; SODIUM STARCH GLYCOLATE TYPE A CORN; TALC; TITANIUM DIOXIDE; ALUMINUM OXIDE

DRUG FACTS

Active ingredient (in each caplet)

Acetaminophen 500 mg

Diphenhydramine HCL 25 mg

Purpose

Pain reliever

Nighttime sleep-aid

Uses

temporarily relief of occasional headaches and minor aches and pains with accompanying sleeplessness.

Warnings

Liver warning: This product contains acetaminophen. Severe liver damage may occur if you take:

- more than 4,000 mg of acetaminophen in 24 hours
- with other drugs containing acetaminophen
- 3 or more alcoholic drinks every day while using this product

Allergy alert: Acetaminophen may cause severe skin reactions. Symptoms may include:

- skin reddening
- blisters
- rash

If a skin reaction occurs, stop use and seek medical help right away.

Do not use

- with any other drug containing acetaminophen (prescription or nonprescription). If you are not sure whether a drug contains acetaminophen, ask a doctor or pharmacist.
- with any other product containing diphenhydramine, even one used on skin
- in children under 12 years of age
- if you have ever had an allergic reaction to this product or any of its ingredients

Ask a doctor before use if you have

- liver disease
- a breathing problem such as emphysema or chronic bronchitis
- trouble urinating due to an enlarged prostate gland
- glaucoma

Ask a doctor or pharmacist before use if you are

- taking the blood thinning drug warfarin
- taking sedatives and tranquilizers

When using this product

- drowsiness will occur
- avoid alcoholic drinks
- do not drive a motor vehicle or operate machinery

Stop use and ask a doctor if

- sleeplessness persists continuously for more than 2 weeks. Insomnia may be a symptom of a serious underlying medical illness
- pain gets worse or lasts more than 10 days
- fever gets worse or lats more than 3 days.
- redness or swelling is present
- new symptoms occur

These could be signs of a serious condition.

If pregnant or breast-feeding,

ask a health professional before use.

Keep out of reach of children.

Overdose warning: In case of overdose, get medical help or contact a Poison Control Center (1-800-222-1222) right away. Quick medical attention is critical for adults as well as for children even if you do not notice any signs or symptoms.

Directions

- do not take more than directed (see Overdose warning)
- adults and children 12 years of age and over: take 2 caplets at bedtime do not take more than 2 caplets of this product in 24 hours
- children under 12 years of age: do not use

Other information

- store between 20-25ºC (68-77ºF)
- avoid high humidity and excessive heat

Inactive ingredients

croscarmellose sodium, FD&C blue #1 aluminum lake,FD&C blue #2 aluminum lake, hypromellose, magnesium stearate, microcrystalline cellulose, polyethylene glycol, polyvinyl alcohol, povidone K 30, pregelatinized starch, purified water, sillcon dioxide, sodium starch glycolate, talc, titanium dioxide

Questions or comments?

Call 1-877-753-3935 Monday-Friday 9AM-5PM EST

Principal Display Panel

Compare to the active ingredients in Extra Strength Tylenol® PM†

extra strength

pain reliever PM

Acetaminophen 500 mg

diphenhydramine HCl 25 mg

pain reliever/nighttime sleep-aid

non habit-forming

for ages 12 years and over

caplets

†This product is not manufactured or distributed by McNeil Consumer Healthcare, distributor of Extra Strength Tylenol® PM.

TAMPER EVIDENT: DO NOT USE IF PRINTED SAFETY SEAL UNDER CAP IS BROKEN OR MISSING.

KEEP OUTER CARTON FOR COMPLETE WARNINGS AND PRODUCT INFORMATION.

Distributed by:

PL Developments

200 Hicks Street, Westbury, NY 11590

Product Label

READYinCASE Extra Strength Pain Reliever PM